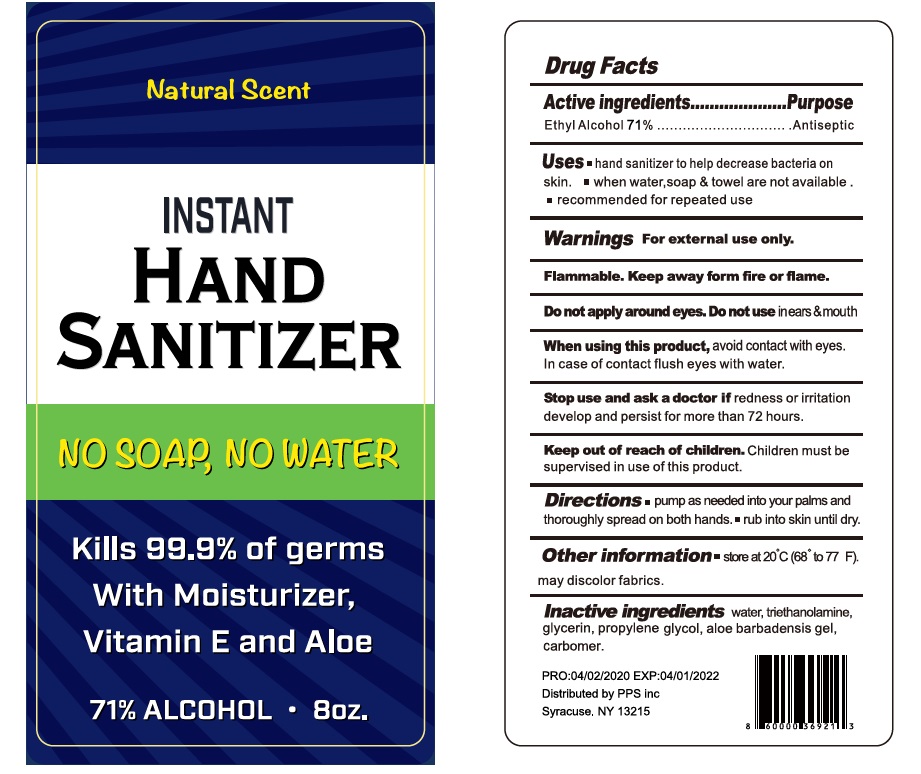 DRUG LABEL: Natural Scent Hand Sanitizer With Moisturizer,  Vitamin E and Aloe
NDC: 75780-010 | Form: GEL
Manufacturer: NINGBO MEINEKE Biotech Technology Co., Ltd.
Category: otc | Type: HUMAN OTC DRUG LABEL
Date: 20200522

ACTIVE INGREDIENTS: alcohol 71 mL/100 mL
INACTIVE INGREDIENTS: WATER; PROPYLENE GLYCOL; ALOE VERA LEAF; CARBOMER 934; GLYCERIN

Drug facts

Active ingredient Purpose

Ethyl Alcohol 71% ... Antiseptic

PURPOSE

- Hand sanitizer to help decrease bacteria on the skin.
- when water, soap and towel are not available.
- recommended for repeated use.

INDICATIONS AND USAGE

keep out of eyes

when water, soap and towel are not available

WARNINGS

For external use only.
Flammable. Keep away from fire or flame.

Do not apply around eyes. Do not use in ears and mouth.

When using this products, avoid contact with eyes. In case of contact, flush eyes with water.

Stop using and ask a doctor, if redness and irritation develop and persist for more than 72 hours.

Other information:

Store at 20℃ （68° to 77℉）.

May discolor fabrics.

KEEP OUT OF REACH OF CHILDREN

Children must be supervised in use of this product.

DOSAGE AND ADMINISTRATION

- pump as needed into your palms and thoroughly spread on both hands
- rub into skin until dry.

INACTIVE INGREDIENT

Water, Triethanolamine, Glycerin, propylene glycol, aloe barbadensis gel, Carbomer